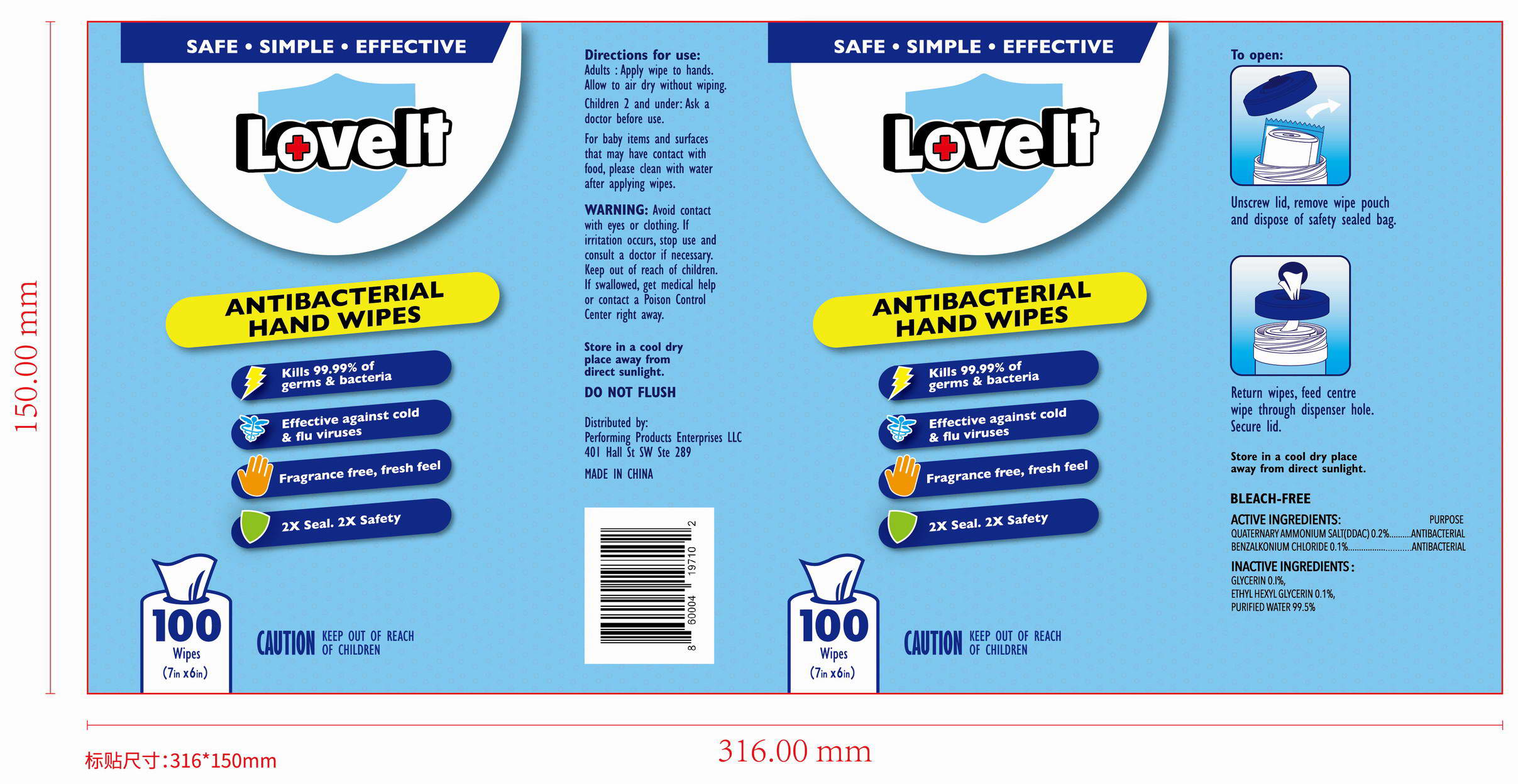 DRUG LABEL: Antibacterial hand wipes
NDC: 78183-030 | Form: CLOTH
Manufacturer: Kunming Ansheng Industry & Trade Co., Ltd.
Category: otc | Type: HUMAN OTC DRUG LABEL
Date: 20200817

ACTIVE INGREDIENTS: QUATERNIUM-18 HECTORITE 0.2 U/100 U; BENZALKONIUM CHLORIDE 0.1 U/100 U
INACTIVE INGREDIENTS: ETHYLHEXYLGLYCERIN 0.1 U/100 U; WATER; GLYCERIN 0.1 U/100 U

Antibacterial hand wipes (Loveit)

Active Ingredient(s)

Quaternary ammonium salt (DDAC) 0.2%v/v;
Benzalkonium Chloride 0.1% v/v.

Purpose

Antibacterial;

Use

For adult: Apply wipe to hands. Allow to air dry without wiping.

Warnings

Warning: Avoid contact with eyes or clothing.

If swallowed, get medical help or contact a poison control center right away.

Do not flush.

Do not use

Children 2 and under: Ask a doctor before use.

WHEN USING

Avoid contact with eyes.

For baby items and surfaces that may have contact with food, Please clean with water after applying wipes.

STOP USE

If irritation occurs, Stop use and consult a doctor.

Keep out of reach of children.

Directions

To open: Unscrew lid, remove wipe pouch and dispose of safety sealed bag.

Return wipes, feed centre wipe through dispenser hole.

Secure lid.

Inactive ingredients

Pure water 99.5%; Glycerol 0.1%; Ethylhexyl glycerin 0.1%.

storage and handling

Store in a cool dry place away from direct sunlight.

Package Label - Principal Display Panel

100 wipes in 1 Canister;
NDC: 78183-030-01;